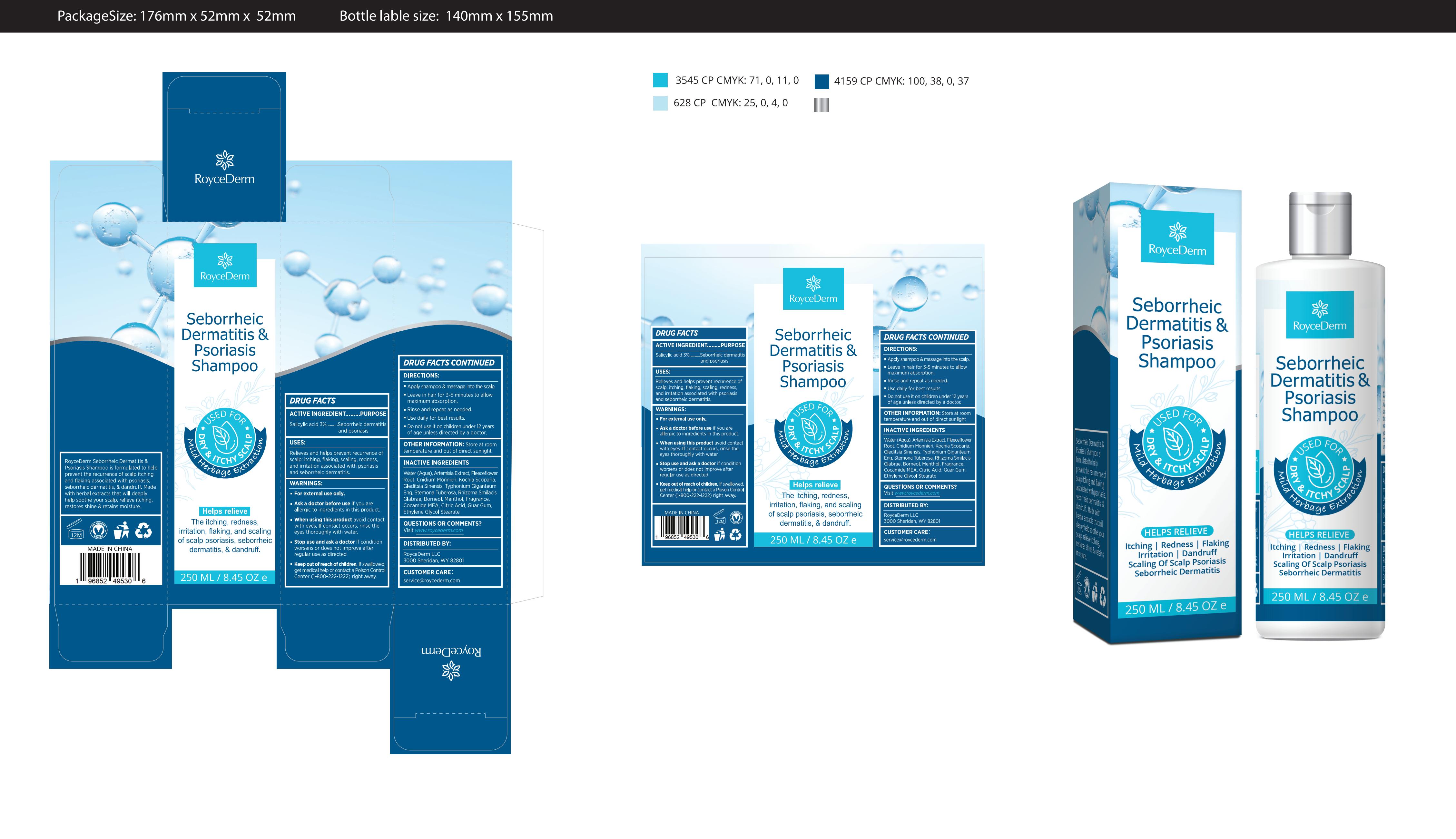 DRUG LABEL: Roycederm Seborrheic Dermatitis Psoriasis Shampoo.
NDC: 84746-002 | Form: SHAMPOO
Manufacturer: Shandong Yuyaotang Pharmaceutical Co., Ltd
Category: otc | Type: HUMAN OTC DRUG LABEL
Date: 20240919

ACTIVE INGREDIENTS: SALICYLIC ACID 3 g/100 mL
INACTIVE INGREDIENTS: FRAGRANCE 13576; COCO MONOETHANOLAMIDE; CITRIC ACID MONOHYDRATE; COPTIS TEETA ROOT; STEMONA TUBEROSA WHOLE; CNIDIUM MONNIERI WHOLE; BORNEOL; MENTHOL; FALLOPIA MULTIFLORA ROOT; SAUROMATUM GIGANTEUM WHOLE; BASSIA SCOPARIA WHOLE; GUAR GUM; GLYCOL CETEARATE; ARTEMISIA ARGYI LEAF; WATER

84746-002

Active Ingredient

Salicylic acid 3%

Purpose

Seborrheic dermatitis and psoriasis.

Use

Relieves and helps prevent recurrence of scalp: itching, flaking, scaling, redness and irritation associated with psoriasis and seborrheic dermatitis.

Warnings

For external use only.

Do not use it on children under 12 years of age unless directed by a doctor.

When Using

avoid contacwith eyes. lf contact occurs, rinse theeyes thoroughly with water.

Stop Use

if conditionworsens or does not improve afterregular use as directed

Ask Doctor

if you areallergic to ingredients in this product

Keep Oot Of Reach Of Children

Do not use it on children under 12 years of age unless directed by a doctor.

Directions

Apply shampoo & massage into the scalp，Leave in hair for 3-5 minutes to allow maximum absorption.Rinse and repeat as needed，Use daily for best results.Do not use it on children under 12 years of age unless directed by a doctor.

Other information

Store at room temperature and out of direct sunlight

Inactive ingredients

Water (Agua), Artemisia Extract, Fleeceflower Root, Cnidium Monnieri, Kochia Scoparia Gleditsia Sinensis, Typhonium Giganteum Eng, Stemona Tuberosa, Rhizoma Smilacis Glabrae, Borneol, Menthol, Fragrance,Cocamide MEA, Citric Acid, Guar Gum，Ethylene Glycol Stearate

Questions

Visit www.roycederm.com